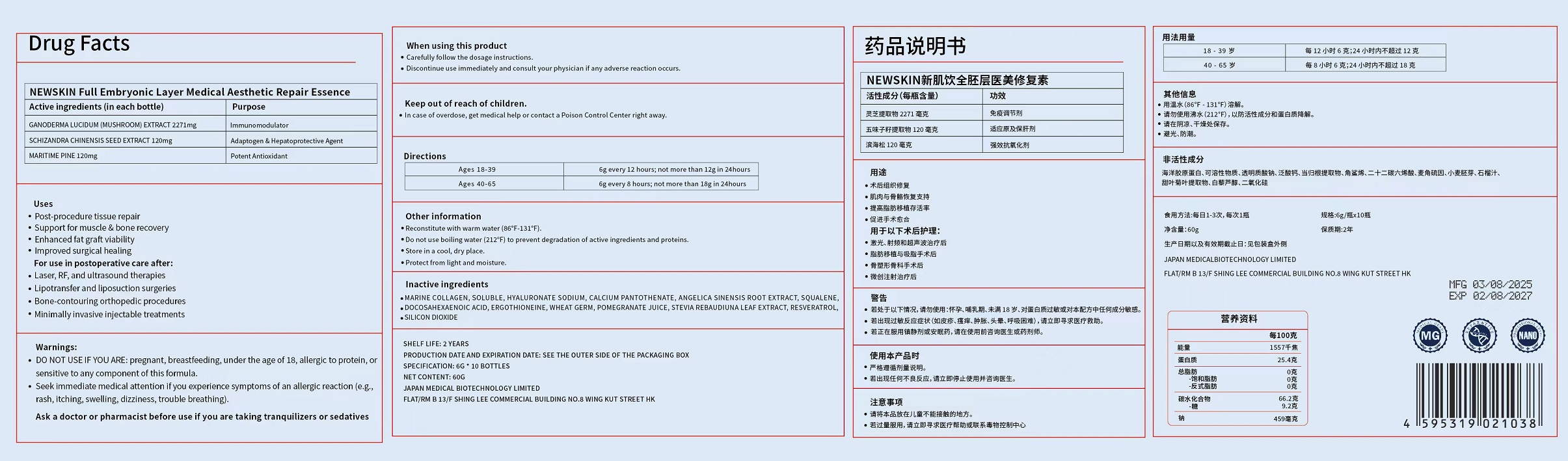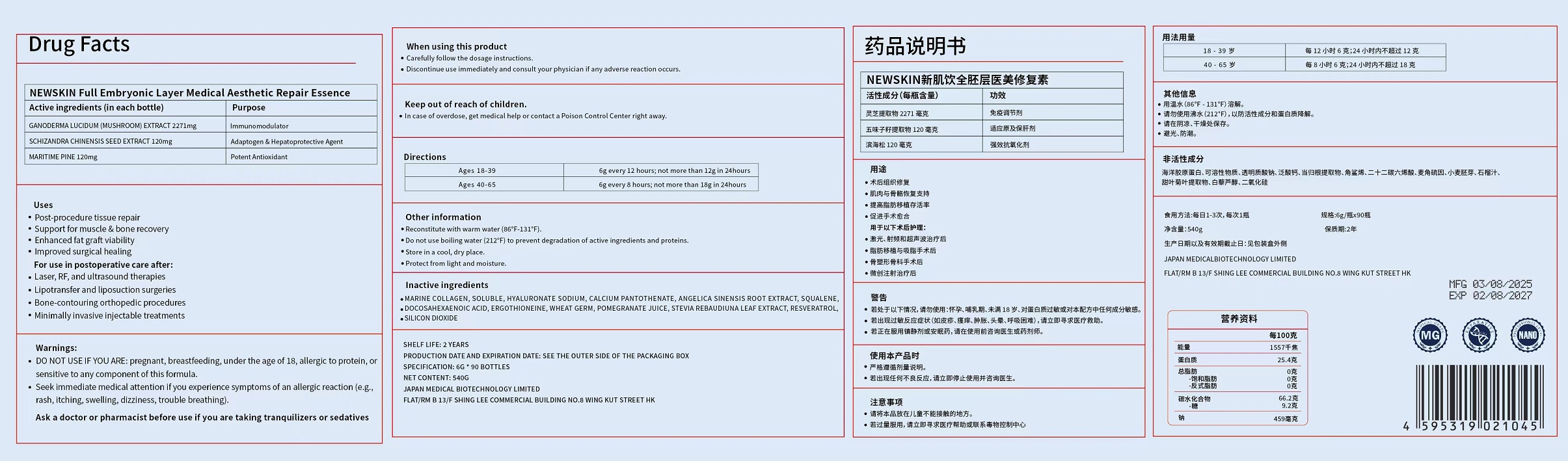 DRUG LABEL: NEWSKIN  Whole-Layer Repair Serum Powder for Post-Aesthetic Skin
NDC: 87130-001 | Form: POWDER
Manufacturer: Japan Medical Biotechnology Limited
Category: otc | Type: HUMAN OTC DRUG LABEL
Date: 20260113

ACTIVE INGREDIENTS: MARITIME PINE 120 mg/6 g; SCHISANDRA CHINENSIS SEED 120 mg/6 g; REISHI 2271 mg/6 g
INACTIVE INGREDIENTS: RESVERATROL; CALCIUM PANTOTHENATE; STEVIA REBAUDIUNA LEAF; HYALURONATE SODIUM; DOCOSAHEXAENOIC ACID; ANGELICA SINENSIS ROOT; MARINE COLLAGEN, SOLUBLE; ERGOTHIONEINE; WHEAT GERM; POMEGRANATE JUICE; SILICON DIOXIDE; SQUALENE

87130-001

Active ingredient（in each tablet）

GANODERMA LUCIDUM (MUSHROOM) EXTRACT 2271mg

SCHIZANDRA CHINENSIS SEED EXTRACT 120mg

MARITIME PINE 120mg

Purpose

Immunomodulator

Adaptogen & Hepatoprotective Agent

Potent Antioxidant

Uses

Post-procedure tissue repair
Support for muscle & bone recovery
Enhanced fat graft viability
Improved surgical healing

For use in postoperative care after:

Laser, RF, and ultrasound therapies
Lipotransfer and liposuction surgeries
Bone-contouring orthopedic procedures
Minimally invasive injectable treatments

Warnings

DO NOT USE IF YOU ARE: pregnant, breastfeeding, under the age of 18, allergic to protein, or sensitive to any component of this formula.

Seek immediate medical attention if you experience symptoms of an allergic reaction (e.g., rash, itching, swelling, dizziness, trouble breathing).

Ask a doctor or pharmacist before use if

you are taking tranquilizers or sedatives

When using this product

Carefully follow the dosage instructions.

Discontinue use immediately and consult your physician if any adverse reaction occurs.

Keep out of reach of children.

In case of overdose,get medical help or contact a Poison Control Center right away.

Directions

Ages 18-39: 6g every 12 hours; not more than 12g in 24hours

Ages 40-65: 6g every 8 hours; not more than 18g in 24hours

Other information

Reconstitute with warm water (86°F-131°F).

Do not use boiling water (212°F) to prevent degradation of active ingredients and proteins.

Store in a cool, dry place.

Protect from light and moisture.

Inactive ingredients

MARINE COLLAGEN, SOLUBLE;HYALURONATE SODIUM;CALCIUM PANTOTHENATE;ANGELICA SINENSIS ROOT EXTRACT;SQUALENE;DOCOSAHEXAENOIC ACID;ERGOTHIONEINE;WHEAT GERM;POMEGRANATE JUICE;STEVIA REBAUDIUNA LEAF EXTRACT;RESVERATROL;SILICON DIOXIDE